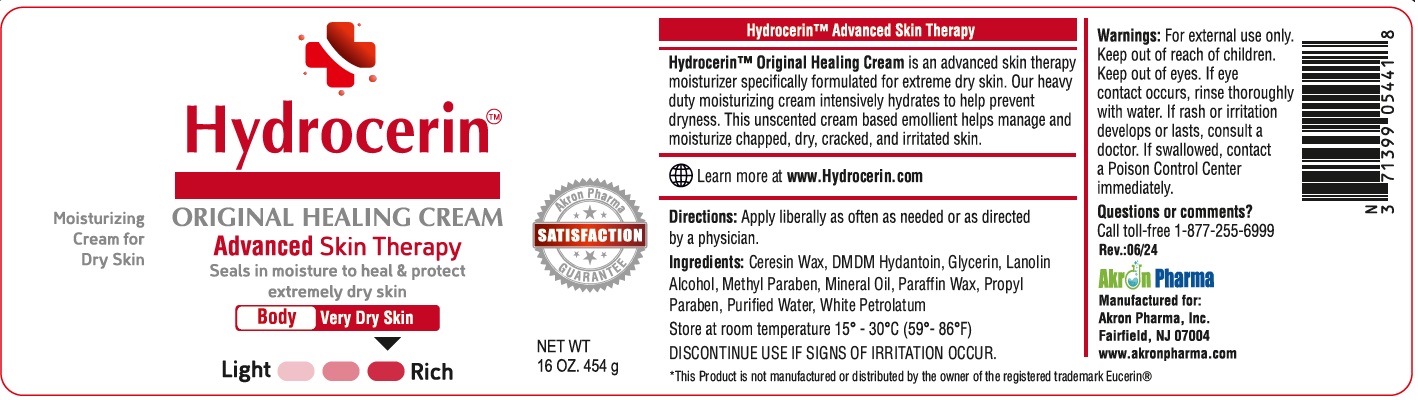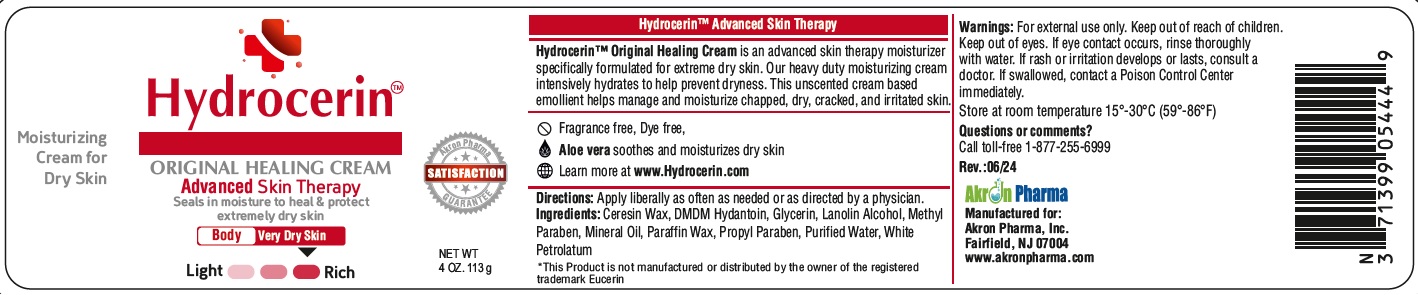 DRUG LABEL: Hydrocerin
NDC: 00371399054418
Manufacturer: AKRON PHARMA INC
Category: other | Type: COSMETIC
Date: 20241212

Hydrocerin
ORIGINAL HEALING CREAM
Advanced Skin Therapy
Seals in moisture to heal & protect
extremely dry skin

Hydrocerin™ Original Healing Cream is an advanced skin therapy moisturizer specifically formulated for extreme dry skin. Our heavy duty moisturizing cream intensively hydrates to help prevent dryness. This unscented cream based emollient helps manage and moisturize chapped, dry, cracked, and irritated skin.

Learn more at www.Hydrocerin.com

Directions: Apply liberally as often as needed or as directed by a physician.

Ingredients: Ceresin Wax, DMDM Hydantoin, Glycerin, Lanolin Alcohol, Methyl Paraben, Mineral Oil, Paraffin Wax, Propyl Paraben, Purified Water, White Petrolatum

DISCONTINUE USE IF SIGNS OF IRRITATION OCCUR

Warnings: For external use only.
Keep out of reach of children.
Keep out of eyes. If eye contact occurs, rinse thoroughly with water. If rash or irritation develops or lasts, consult a doctor. If swallowed, contact
a Poison Control Center immediately.
Questions or comments?
Call toll-free 1-877-255-6999

Manufactured for:

Akron Pharma, Inc.
Fairfield, NJ 07004

www.akronpharma.com

Made in USA